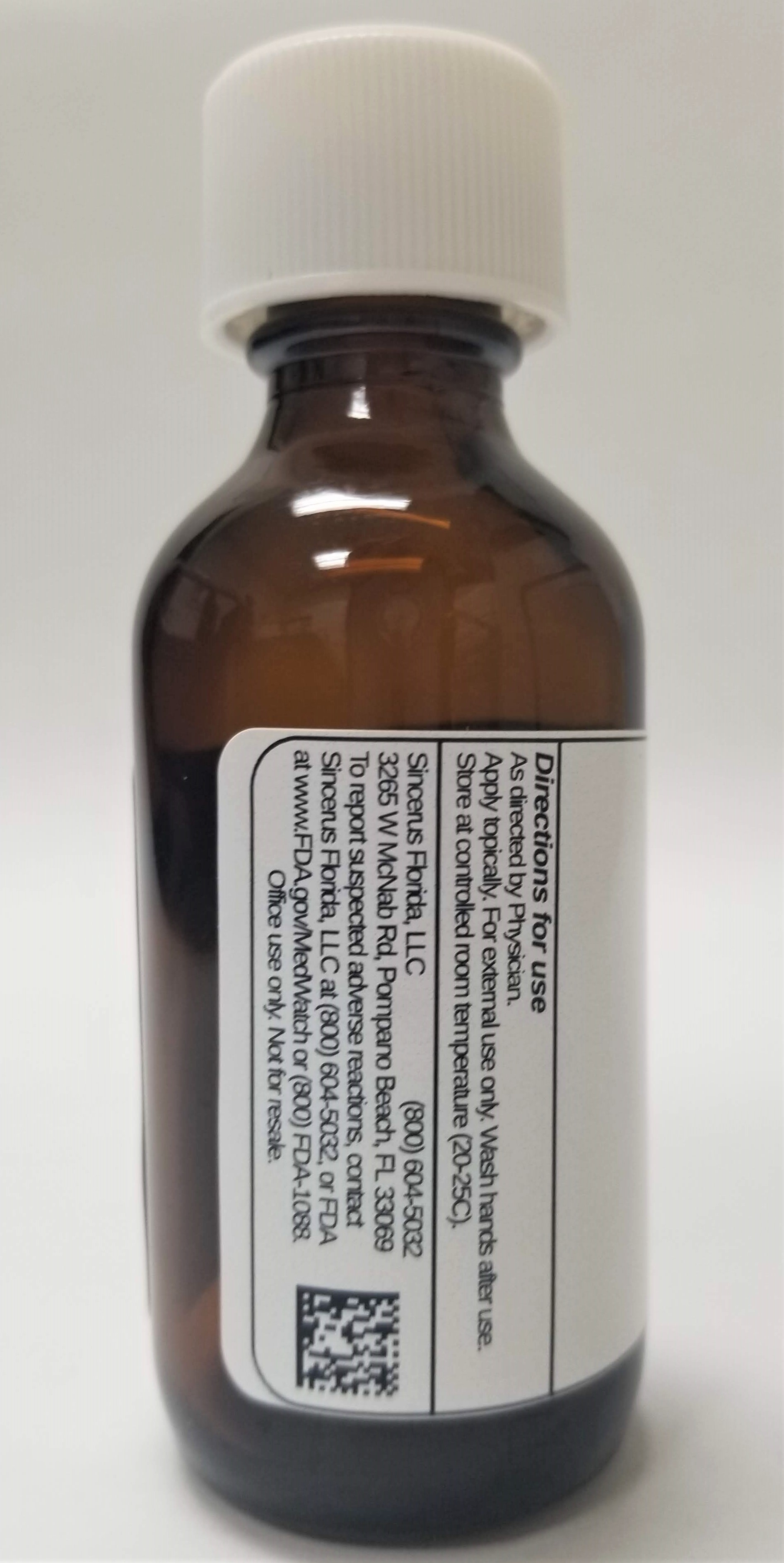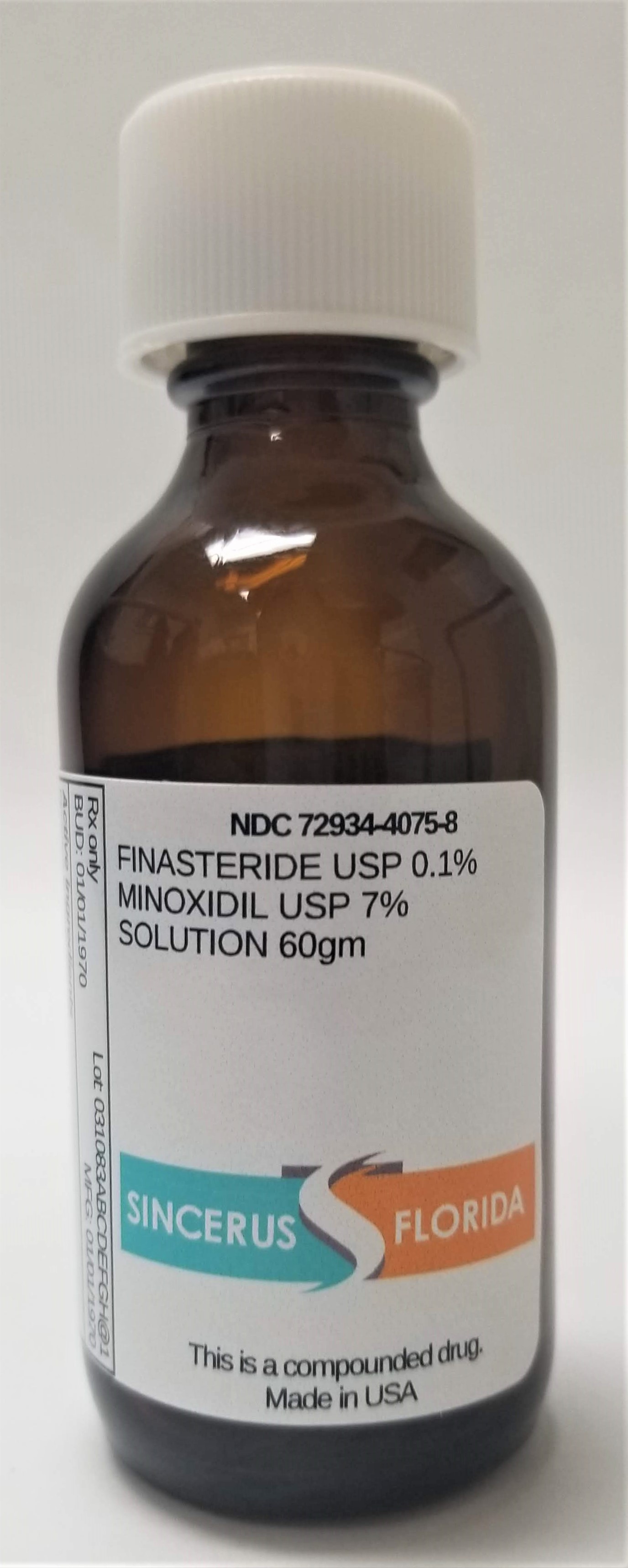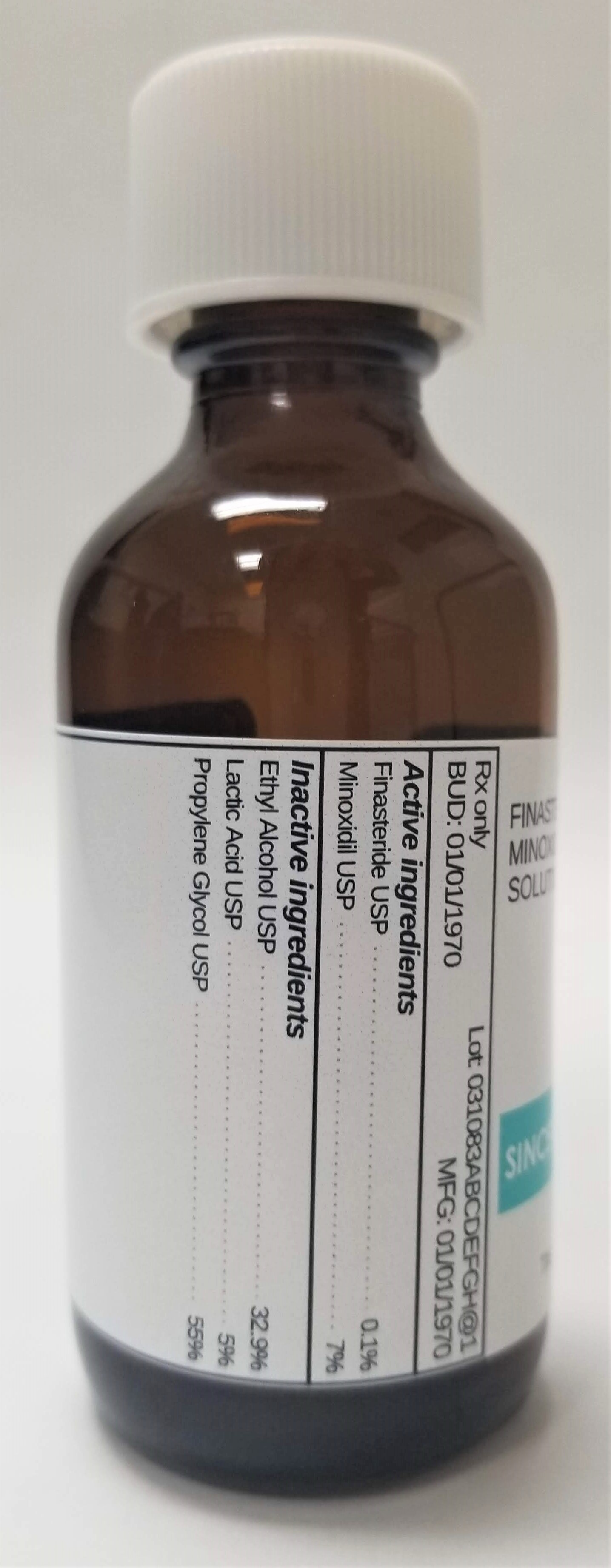 DRUG LABEL: FINASTERIDE 0.1% / MINOXIDIL 7%
NDC: 72934-4075 | Form: SOLUTION
Manufacturer: Sincerus Florida, LLC
Category: prescription | Type: HUMAN PRESCRIPTION DRUG LABEL
Date: 20190424

ACTIVE INGREDIENTS: FINASTERIDE 0.1 g/100 g; MINOXIDIL 7 g/100 g

FINASTERIDE 0.1% / MINOXIDIL 7%